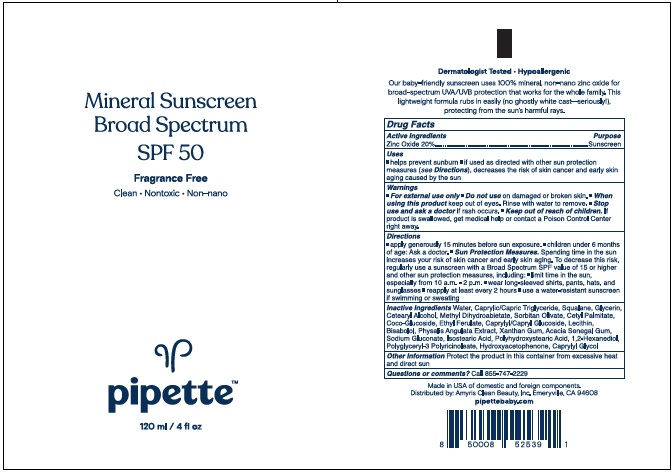 DRUG LABEL: Pipette Mineral Sunscreen Broad Spectrum
NDC: 73517-382 | Form: LOTION
Manufacturer: Amyris, Inc
Category: otc | Type: HUMAN OTC DRUG LABEL
Date: 20221103

ACTIVE INGREDIENTS: ZINC OXIDE 20 g/100 mL
INACTIVE INGREDIENTS: WATER; MEDIUM-CHAIN TRIGLYCERIDES; GLYCERIN; SQUALANE; CETOSTEARYL ALCOHOL; METHYL DIHYDROABIETATE; SORBITAN OLIVATE; CETYL PALMITATE; COCO GLUCOSIDE; ETHYL FERULATE; ISOSTEARIC ACID; LECITHIN, SOYBEAN; POLYGLYCERYL-3 RICINOLEATE; POLYHYDROXYSTEARIC ACID (2300 MW); CAPRYLYL/CAPRYL OLIGOGLUCOSIDE; ACACIA SENEGAL WHOLE; XANTHAN GUM; SODIUM GLUCONATE; BISABOLOL OXIDE A; HYDROXYACETOPHENONE; HEXANEDIOL; CAPRYLYL GLYCOL; PHYSALIS ANGULATA

Active Ingredients

Zinc Oxide 20%

Purpose

Sunscreen

Uses

Helps prevent sunburn

if used as directed with other sun protection measures(see directions), decreases the risk of skkin cancer and early signs of aging caused by the sun.

Warnings

For external use only

Do not use

on damaged of broken skin

When using this product

keep out of eyes. Rinse with water to remove

Stop use and ask

a doctor if rash occurs

Keep out of reach of children

If product is swallowed, get medical help or contact a Poison Control Center right away.

Directions

- Apply generously 15 minutes before sun exposure
- reapply at least every 2 hours
- Sun Protection Measures Spending time in the sun increases your risk of skin cancer and early skin aging. To decrease this risk, regularyly use a sunscreen with a Broad Spectrum value of SPF 15 or higher and other sun protection measures including
- Limit time in the sun, especially from 10 a.m.- 2 p.m.
- wear long-sleeved shiirts, pants, hats and sunglasses
- use a water-resistant sunscreen if swimming or sweating
- children under 6 months of age:ask a doctor.

Inactive ingredients

Water, Caprylic/Capric Triglyceride, Glycerin, Squalane, Cetearyl Alcohol, Methyl Dihydroabietate, Sorbitan Olivate, Cetyl Palmitate, Coco-Glucoside, Ethyl Ferulate, Bisabolol, Hydroxyacetophenone, Isostearic Acid, Lecithin, Polyglyceryl-3 Polyricinoleate, Polyhydroxystearic Acid, Caprylyl/Capryl Glucosides, 1,2-Hexandiol, Caprylyl Glycol, Physalis Angulata Extract, Acacia Senegal Gum, Xanthan Gum, Sodium Gluconate.